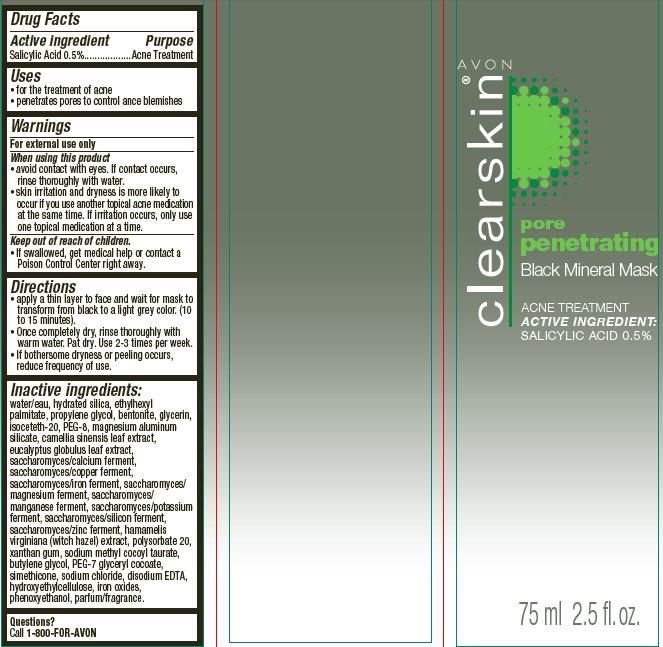 DRUG LABEL: Clearskin Pore Penetrating
NDC: 10096-0297 | Form: PASTE
Manufacturer: New Avon LLC
Category: otc | Type: HUMAN OTC DRUG LABEL
Date: 20190101

ACTIVE INGREDIENTS: SALICYLIC ACID 5 mg/1 mL
INACTIVE INGREDIENTS: WATER

Clearskin Pore Penetrating Black Mineral Mask

Active ingredient
Salicylic Acid 0.50%.........................................

Purpose
..................................................Acne Treatment

Uses
• for the treatment of acne
• penetrates pores to control ance blemishes

Warnings
For external use only.

When using this product
• avoid contact with eyes. If contact occurs, rinse thoroughly with water.
• skin irritation and dryness is more likely to occur if you use another topical acne medication at the same time. If irritation occurs, only use
one topical medication at a time.

Keep out of reach of children.

- If swallowed, get medical help or contact a Poison Control Center right away.

Directions

• apply a thin layer to face and wait for mask to transform from black to a light grey color. (10 to 15 minutes).
• Once completely dry, rinse thoroughly with warm water. Pat dry. Use 2-3 times per week.
• If bothersome dryness or peeling occurs, reduce frequency of use.

Inactive ingredients
water/eau, hydrated silica, ethylhexyl palmitate, propylene glycol, bentonite, glycerin, isoceteth-20, PEG-8, magnesium aluminum silicate, camellia sinensis leaf extract, eucalyptus globulus leaf extract, saccharomyces/calcium ferment, saccharomyces/copper ferment, saccharomyces/iron ferment, saccharomyces/ magnesium ferment, saccharomyces/manganese ferment, saccharomyces/potassium ferment, saccharomyces/silicon ferment, saccharomyces/zinc ferment, hamamelis virginiana (witch hazel) extract, polysorbate 20, xanthan gum, sodium methyl cocoyl taurate, butylene glycol, PEG-7 glyceryl cocoate, simethicone, sodium chloride, disodium EDTA, hydroxyethylcellulose, iron oxides, phenoxyethanol, parfum/fragrance.

Questions? Call 1-800-FOR-AVON